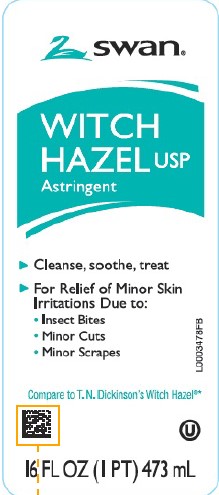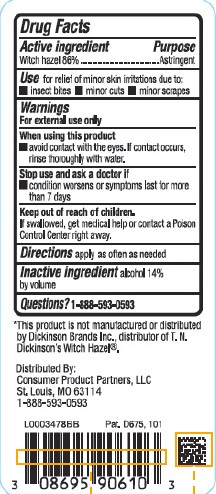 DRUG LABEL: Witch Hazel
NDC: 11344-822 | Form: LIQUID
Manufacturer: Consumer Product Partners, LLC
Category: otc | Type: HUMAN OTC DRUG LABEL
Date: 20250227

ACTIVE INGREDIENTS: WITCH HAZEL 860 mg/1 mL
INACTIVE INGREDIENTS: ALCOHOL

Swan 822.001/822AA
Witch Hazel

Active ingredients

Witch hazel 86%

Purpose

Astringent

Use

for relief of minor skin irritations due to:
• insect bites •minor cuts •minor scrapes

Warnings

For external use only

When using this product

- avoid contact with the eyes. If contact occurs, rinse thoroughly with water.

Stop use and ask a doctor if

- condition worsens or symptoms last for more than 7 days

Keep out of reach of children.

If swallowed, get medical help or contact a Poison Control Center right away.

Directions

apply as often as needed

Inactive ingredient

alcohol 14% by volume

Disclaimer

*This product is not manufactured or distributed by Dickinson Brands, Inc. distributor of T.N. Dickinson's Witch Hazel®.

Adverse reaction

Distributed by:

Consumer Product Partners, LLC

St. Louis, MO 63114

1-888-593-0593

Pat. D675,101

Principal display panel

swan®

WITCH HAZEL USP

Cleanse, soothe, treat

For Relief of Minor Skin Irritations Due to:

- Insect Bites
- Minor Cuts
- Minor Scrapes

Compare to T.N. Dickinson's Witch Hazel®*

16 FL OZ (1 PT) 473 mL